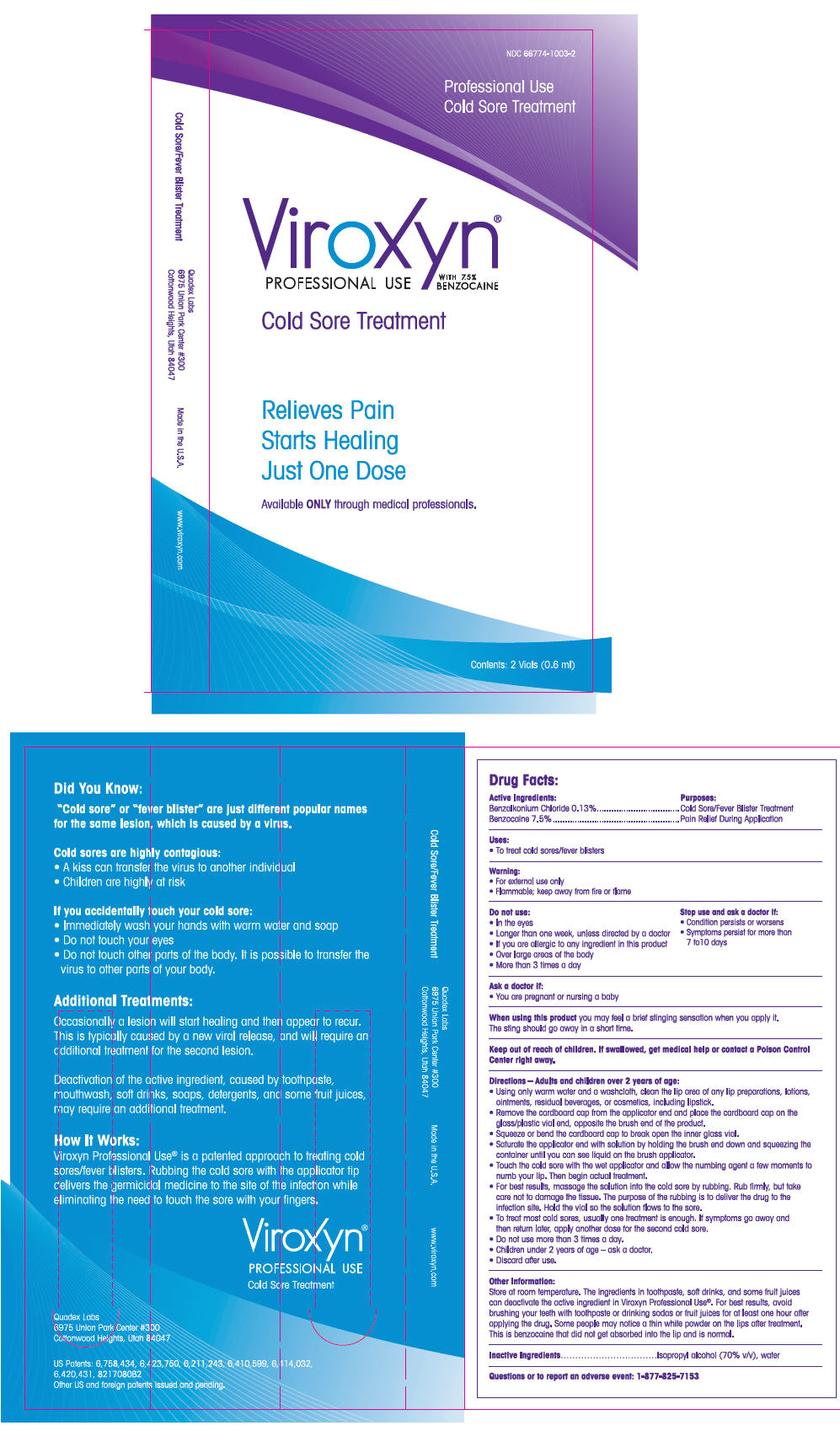 DRUG LABEL: Viroxyn Professional Use
NDC: 66774-1003 | Form: LIQUID
Manufacturer: Quadex Pharmaceuticals LLC
Category: otc | Type: HUMAN OTC DRUG LABEL
Date: 20121102

ACTIVE INGREDIENTS: Benzalkonium chloride 1.14 mg/1 mL; Benzocaine 65.775 mg/1 mL
INACTIVE INGREDIENTS: Isopropyl Alcohol; Water

Viroxyn® Professional Use

Drug Facts

ACTIVE INGREDIENT

PURPOSE

Active Ingredients: | Purposes:
Benzalkonium Chloride 0.3% | Cold Sore/Fever Blister Treatment
Benzocaine 7.5% | Pain Relief During Application

Uses

- To treat cold sores/fever blisters.

Warning

- For external use only.
- Flammable; keep away from fire or flame

Do not use

- In the eyes
- Longer than one week, unless directed by a doctor
- If you are allergic to any ingredient in this product
- Over large areas of the body
- More than 3 times a day

Stop use and ask a doctor if:

- Condition persists or worsens
- Symptoms persist for more than 7-10 days

Ask a doctor if:

- You are pregnant or nursing a baby

When using this product you may feel a brief stinging sensation when you apply it. The sting should go away in a short time.

Keep out of reach of children. If swallowed, get medical help or contact a Poison Control Center right away.

Directions – Adults and children over 2 years of age

- Using only warm water and a washcloth, clean the lip area of any lip preparations, lotions, ointments, residual beverages, or cosmetics, including lipstick.
- Remove the cardboard cap from the applicator end and place the cardboard cap on to the glass/plastic vial end, opposite the brush end of the product.
- Squeeze the cardboard cap to break open the inner glass vial.
- Saturate the applicator end with solution by holding the brush end down and squeezing the container until you can see liquid on the brush applicator.
- Touch the cold sore with the wet applicator and allow the numbing agent a few moments to numb your lip. Then begin actual treatment.
- For best results, message the solution into the cold sore by rubbing. Rub firmly, but take care not to damage the tissue. The purpose of the rubbing is to deliver the drug to the infection site. Hold the vial so the solution flows to the sore.
- To treat most cold sores, usually one treatment is enough. If you symptoms go away and then return later, apply another dose for the second cold sore.
- Do not use more than 3 times a day.
- Children under 2 years of age – ask a doctor or dentist.
- Discard after use.

Other Information

Store at room temperature. The ingredients in toothpaste, soft drinks, and some fruit juices can deactivate the active ingredient in Viroxyn Professional Use®. For best results, avoid brushing your teeth with toothpaste or drinking sodas or fruit juices for at least one hour after applying the drug. Some people may notice a thin white powder on the lips after treatment. This is benzocaine that did not get absorbed into the lip and is normal.

Inactive Ingredients

Isopropyl alcohol (70% v/v), water

QUESTIONS

Questions or to report an adverse event: 1-877-825-7153

Quadex Labs
6975 Union Park Center #300
Salt Lake City, Utah 84047
www.viroxyn.com
1-877-825-7153

PRINCIPAL DISPLAY PANEL - 2 Vial Carton

NDC 66774-1003-2

Professional Use
Cold Sore Treatment

Viroxyn®
PROFESSIONAL USE
WITH 7.5%
BENZOCAINE

Cold Sore Treatment

Relieves Pain
Starts Healing
Just One Dose

Available ONLY through medical professionals.

Contents: 2 Vials (0.6 ml)